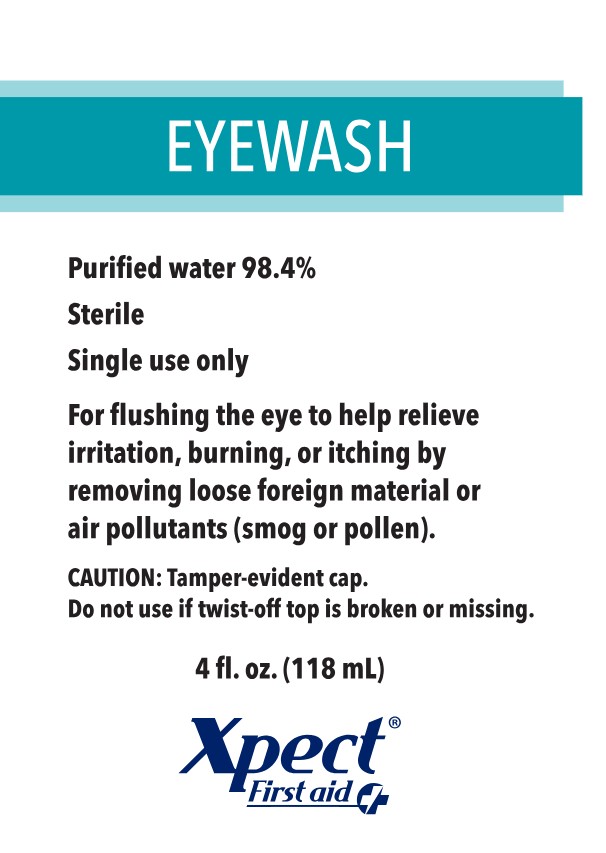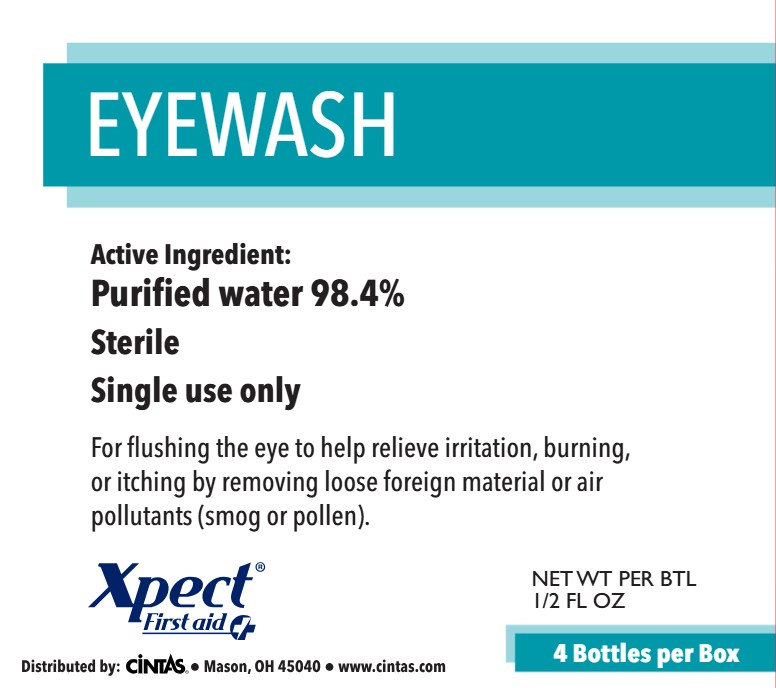 DRUG LABEL: Xpect Eyewash
NDC: 42961-231 | Form: SOLUTION
Manufacturer: Cintas Corporation
Category: otc | Type: HUMAN OTC DRUG LABEL
Date: 20250930

ACTIVE INGREDIENTS: WATER .984 mL/1 mL
INACTIVE INGREDIENTS: BORIC ACID; SODIUM CHLORIDE; SORBIC ACID; SODIUM BORATE

Xpect Eyewash

Active ingredient

Purified water 98.4%

Purpose

Eyewash

INDICATIONS AND USAGE

Uses For cleansing the eye to help relieve irritation by removing loose foreign material, air pollutants (smog or pollen), or chlorinated water.

Warnings

For external use only

- To avoid contamination, do not touch tip of container to any surface. Do not reuse. Once opened, discard
- Remove contact lenses before using
- If you experience eye pain, changes in vision, continued redness or irritation of the eye, or if the condition worsens or persists, consult a doctor
- Obtain immediate medical treatment for all open wounds in or near the eyes
- If solution changes color or becomes cloudy do not use

Keep out of reach of children. If swallowed, get medical help or contact a Poison Control Center right away.

Directions

- Twist off top to open
- Flush the affected eye as needed, controlling the rate of flow of solution by pressure on the bottle
- Discard bottle after use

Other information

- Store at 5°C to 29.4°C [41° to 85°F]
- Do not use if top is broken or missing
- Lot number and expiration date are embossed on bottle

INACTIVE INGREDIENT

Inactive ingredients boric acid, sodium borate, sodium chloride, sorbic acid

Questions or comments?

Call 1-877-973-2811 M-F 8 am-5 pm

Principal Display Panel - 118mL Bottle

EYEWASH

Purified water 98.4%

Sterile

Single use only

For flushing the eye to help relieve irritation, burning, or itching by removing loose foreign material or air pollutants (smog or pollen).

CAUTION: Tamper-evident cap. Do not use if twist-off top is broken or missing.

4 fl. oz. (118 mL)

Xpect® First aid

Principal Display Panel - 4 Count Box

EYEWASH

Active Ingredient:

Purified water 98.4%

Sterile

Single use only

For flushing the eye to help relieve irritation, burning, or itching by removing loose foreign material or air pollutants (smog or pollen).

Xpect® First aid

Distributed by: Cintas® • Mason, OH 45040 • www.cintas.com

NET WT PER BTL 1/2 FL OZ

4 Bottles per Box